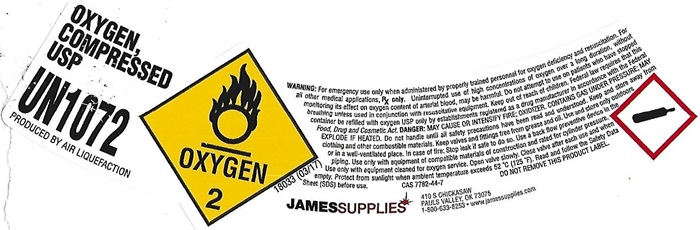 DRUG LABEL: OXYGEN
NDC: 50505-001 | Form: GAS
Manufacturer: James Supplies, L.L.c
Category: prescription | Type: HUMAN PRESCRIPTION DRUG LABEL
Date: 20241027

ACTIVE INGREDIENTS: OXYGEN 99 L/100 L

OXYGEN COMPRESSED LABEL

OXYGEN, COMPRESSED USP UN 1072

PRODUCED BY AIR LIQUEFACTION

OXYGEN 2 18033 (03/17)

WARNING: For emergency use only when administered by properly trained personnel for oxygen deficiency and resuscitation. For all other medical applications, Rx only. Uninterrupted use of high concentrations of oxygen over a long duration, without monitoring its effect on oxygen content of arterial blood, may be harmful. Do not attempt to use on patients who have stopped breathing unless used in conjunction with resuscitative equipment. Produced by Air Liquefaction. DANGER: MAY CAUSE OR INTENSIFY FIRE; OXIDIZER. CONTAINS GAS UNDER PRESSURE; MAY EXPLODE IF HEATED. Do not handle until all safety precautions have been read and understood. Keep and store away from clothing and other combustible materials. Keep valves and fittings free from grease and oil. Use and store only outdoors or in a well-ventilated place. In case of fire: Stop leak if safe to do so. Use a back flow preventive device in the piping. Use only with equipment of compatible materials of construction and rated for cylinder pressure. Use only with equipment cleaned for oxygen service. Open valve slowly. Close valve after each use and when empty. Protect from sunlight when ambient temperature exceeds 52°C (125° F). Read and follow the Safety Data Sheet (SDS) before use. CAS 7782-44-7 DO NOT REMOVE THIS PRODUCT LABEL.

JAMESSUPPLIES

410 S CHICKASAW

PAULS VALLEY, OK 73075

1-800-633-5253 • www.jamessupplies.com